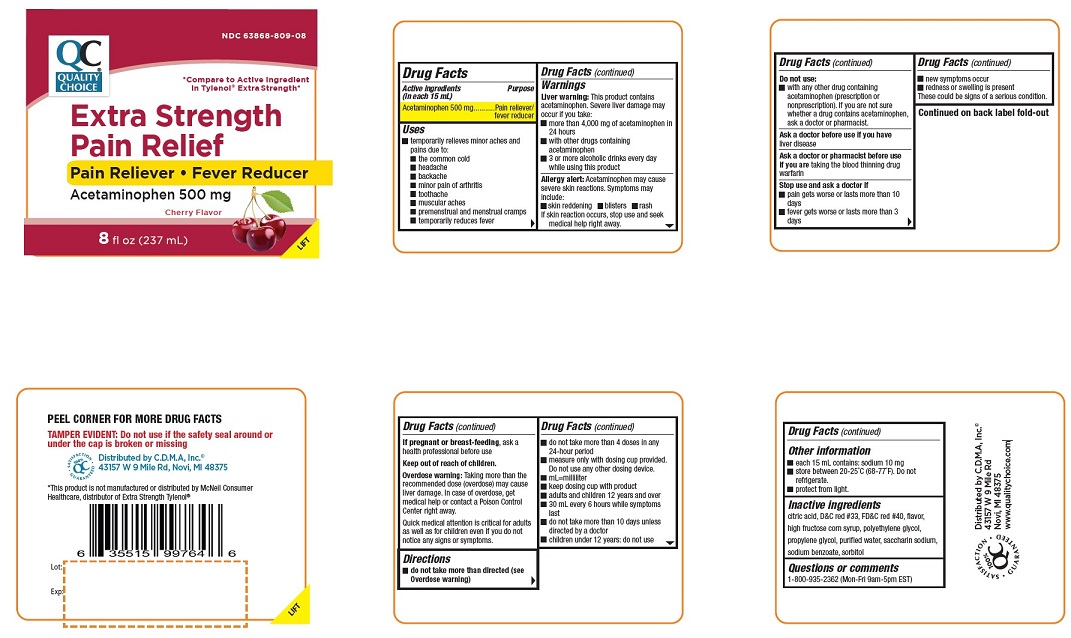 DRUG LABEL: Acetaminophen
NDC: 63868-809 | Form: SYRUP
Manufacturer: CHAIN DRUG MARKETING ASSOCIATION INC.
Category: otc | Type: HUMAN OTC DRUG LABEL
Date: 20241226

ACTIVE INGREDIENTS: ACETAMINOPHEN 500 mg/15 mL
INACTIVE INGREDIENTS: CITRIC ACID MONOHYDRATE; D&C RED NO. 33; FD&C RED NO. 40; HIGH FRUCTOSE CORN SYRUP; PROPYLENE GLYCOL; POLYETHYLENE GLYCOL, UNSPECIFIED; WATER; SODIUM BENZOATE; SORBITOL; SACCHARIN SODIUM

Active Ingredient Purpose

(In each 15 mL)

in Acetaminophen 500 mg............. Pain reliever/fever reducer

PURPOSE

- Pain Reliever
- Fever Reducer

Uses

- temporarily relieves minor aches and pains due to:
  - the common cold
  - headache
  - backache
  - minor pain of arthritis
  - toothache
  - muscular aches
  - premenstrual and menstrual cramps
  - temporarily reduces fever

Warnings

Liver warning: This product contains acetaminophen. Severe liver damage may occur if you take:

- more than 4,000 mg of acetaminophen in 24 hours
- with other drugs containing acetaminophen
- 3 or more alcoholic drinks every day while using this product

Allergy alert: Acetaminophen may cause severe skin reactions. Symptoms may include:

- skin reddening
- blisters
- rash

if skin reaction occurs, stop use and seek medical help right away.

Do not use

- with any other drug containing acetaminophen (prescription or nonprescription). If you are not sure whether a drug contains acetaminophen, ask a doctor or pharmacist.
- if your child is allergic to acetaminophen or any of the inactive ingredients in this product.

Ask a doctor before use if you have

liver disease.

Ask a doctor or pharmacist before use if you are taking the blood thinning drug warfarin.

Stop use and ask a doctor if

- pain gets worse or lasts more than 10 days
- fever gets worse or lasts more than 3 days
- new sympthoms occur
- redness or swelling is present

These could be signs of a serious condition.

PREGNANCY OR BREAST FEEDING

If pregnant or breast-feeding, ask a health professional before use

Keep out of reach of children.

OVERDOSAGE

Overdose warning: Taking more than the recommended dose (overdose) may cause liver damage. In case of overdose, get medical help or contact a Poison Control Center right away.

Quick medical attention is critical for adults as well as for children even if you do not notice any signs or symptoms.

Directions

- do not take more than directed (see Overdose warning)
- do not take more than 4 doses in any 24-hour period
- measure only with dosing cup provided. Do not use any other dosing device.
- mL=milliliter
- keep dosing cup with product
- adults and children 12 years and over
- 30 mL every 6 hours while symptoms last
- do not take more than 10 days unless directed by a doctor
- children under 12 years: do not use

Other information

- each 15 mL contains: sodium 10 mg
- store between 20-25°C (68-77°F). Do not refrigerate.
- protect from light.

Questions or comments
1-800-935-2362 (Mon-Fri 9am-5pm EST)

Inactive ingredients

citric acid, D&C red #33, FD&C red #40, flavor, high fructose corn syrup, polyethylene glycol, propylene glycol, purified water, saccharin sodium,
sodium benzoate, sorbitol

- TAMPER EVIDENT: Do not use if the safety seal around or under the cap is broken or missing
- *Compare to Active Ingredient in Tylenol® Extra Strength*
- *This product is not manufactured or distributed by McNeil Consumer Healthcare, distributor of Extra Strength Tylenol®

Distributed by C.D.M.A, Inc.©
43157 W 9 Mile Rd
Novi, MI 48375
www.qualitychoice.com